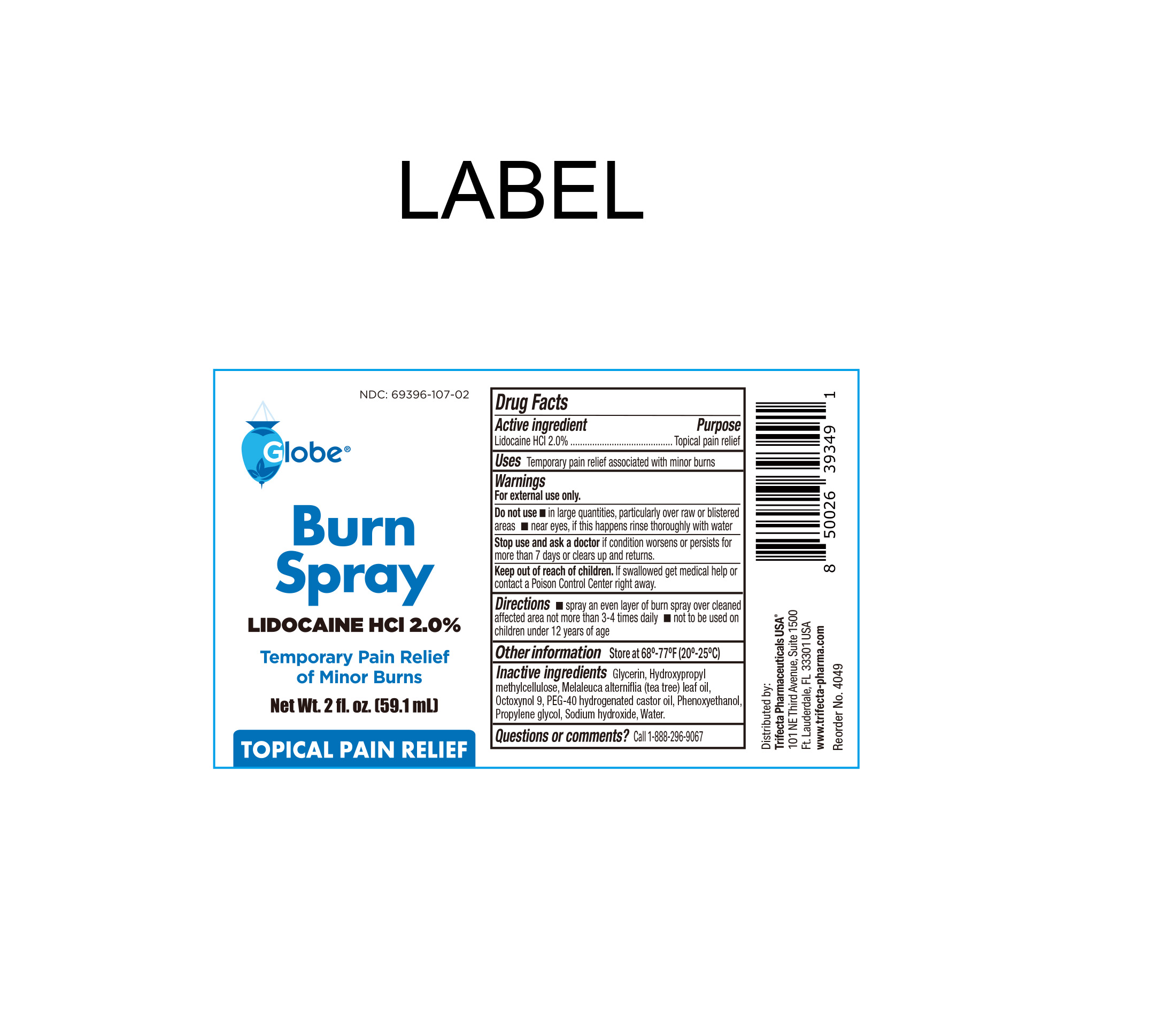 DRUG LABEL: Burn Relief
NDC: 69396-107 | Form: SPRAY
Manufacturer: Trifecta Pharmaceuticals USA, LLC.
Category: otc | Type: HUMAN OTC DRUG LABEL
Date: 20240712

ACTIVE INGREDIENTS: LIDOCAINE HYDROCHLORIDE 20 g/1 L
INACTIVE INGREDIENTS: WATER; GLYCERIN; TEA TREE OIL; PHENOXYETHANOL; PROPYLENE GLYCOL; OCTOXYNOL-9; POLYOXYL 40 HYDROGENATED CASTOR OIL; SODIUM HYDROXIDE; HYPROMELLOSES

Burn Spray

Active Ingredient

Lidocaine HCI 2.0%

Purpose

Topical Pain Relief

INDICATIONS AND USAGE

Temporary pain relief associated with minor burns.

Warnings

For External Use Only

Stop use and ask a doctor

- If the condition worsens or persists for more than 7 days or clears up and returns.

Keep out of the reach of children

If swallowed, get medical help or contact a Poison Control Center right away.

Do Not Use

- In large quantities, particularly over raw or blistered areas
- Near eyes, if this happens rinse throughly with water

Directions

- Spray an even layer of burn spray over cleaned affected area not more than 3-4 times daily.
- Not to be used on children under 12 years of age.

Other information

- Store at controlled room temperature 68º-77ºF (20º-25ºC)

Inactive Ingredients

Glycerin, hydroxypropyl methylcellulose, melaleuca alternifilia (tea tree) leaf oil, octoxynol 9, PEG-40 hydrogenated castor oil, phenoxyethanol propylene glycol, triethanolamine, water

Questions or Comments

Call 1-888-296-9067

Distributed By:

Trifecta Pharmaceuticals USA, LLC.

101 NE Third Avenue, Suite 1500

Ft. Lauderdale, FL. 33301 USA

www.trifecta-pharma.com

SKU: 4049